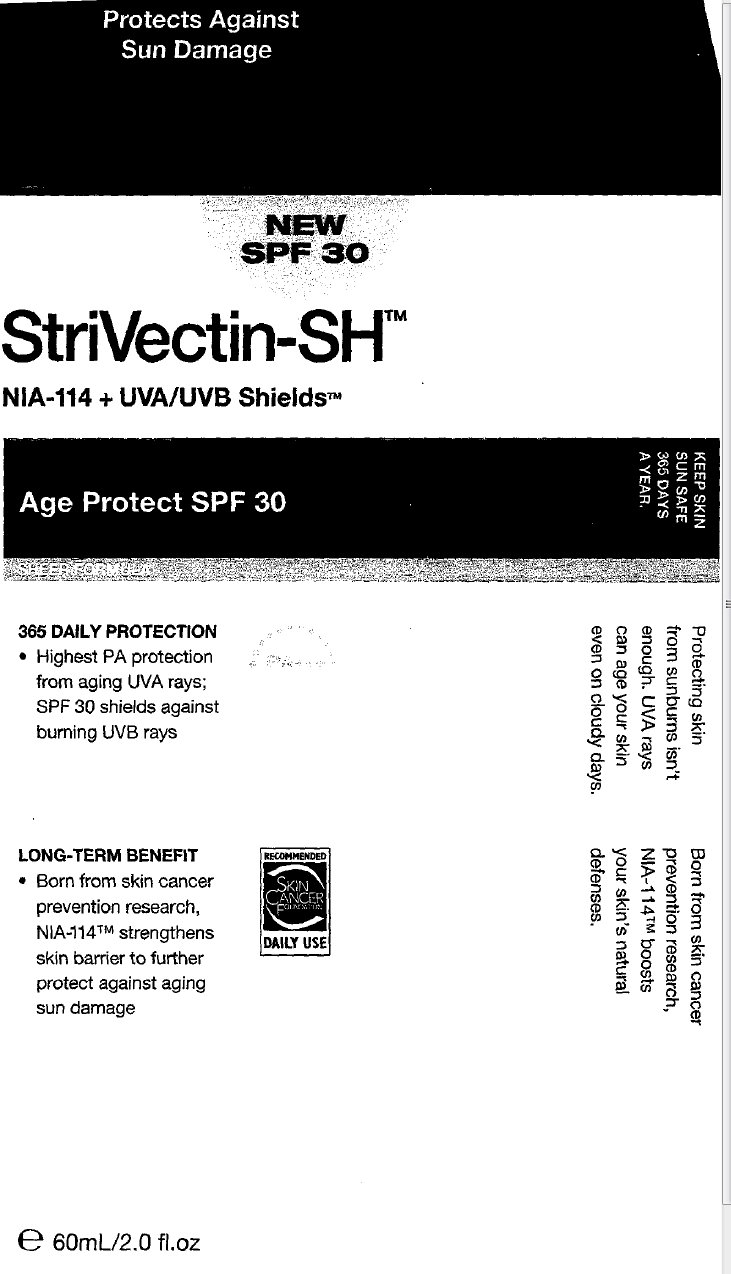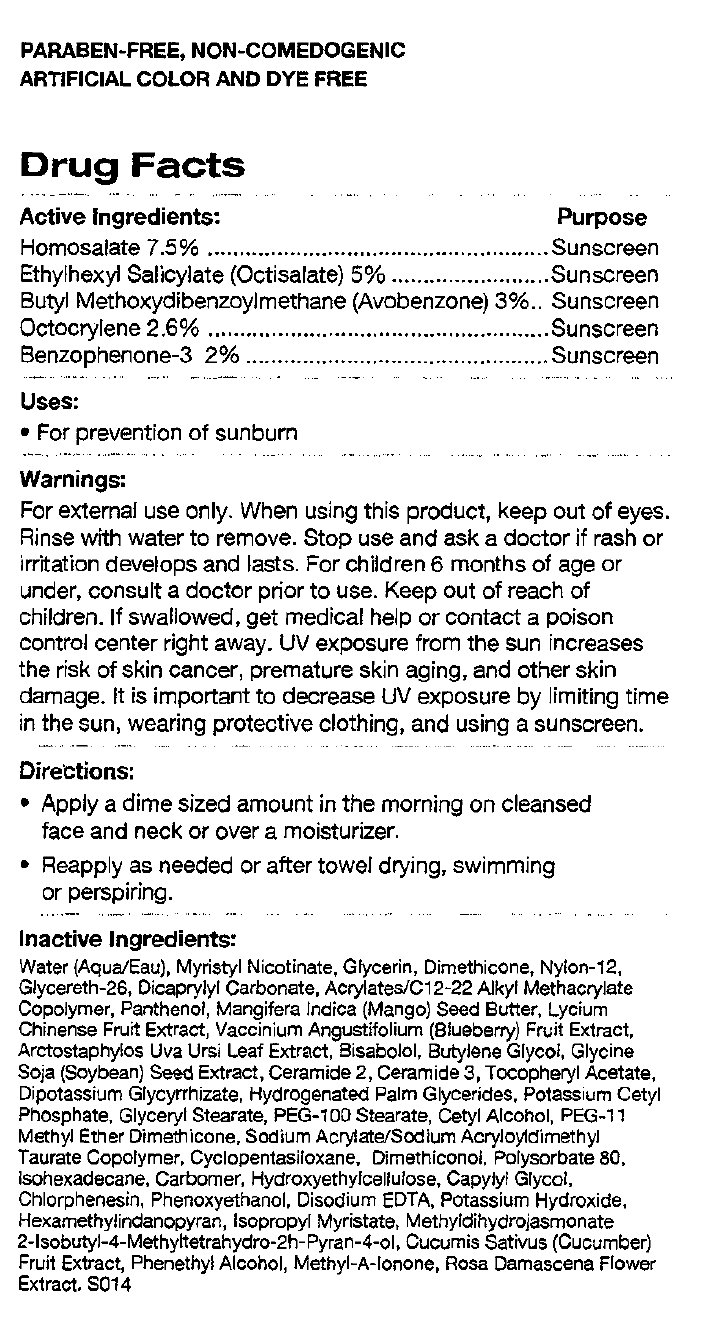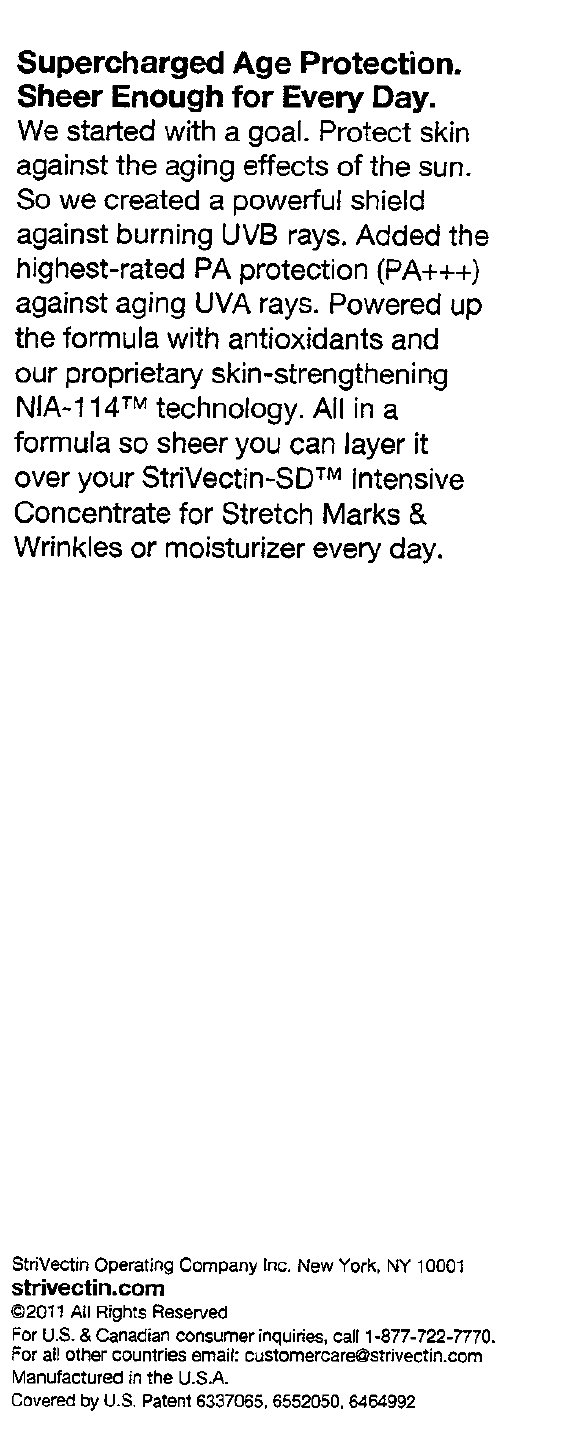 DRUG LABEL: StriVectin-SH NIA-114 UVA UVB Shields SPF 30
NDC: 76147-123 | Form: CREAM
Manufacturer: StriVectin Operating Company Inc.
Category: otc | Type: HUMAN OTC DRUG LABEL
Date: 20251226

ACTIVE INGREDIENTS: HOMOSALATE 75 mg/1 mL; OCTISALATE 50 mg/1 mL; AVOBENZONE 30 mg/1 mL; OCTOCRYLENE 26 mg/1 mL; OXYBENZONE 20 mg/1 mL
INACTIVE INGREDIENTS: WATER; MYRISTYL NICOTINATE; GLYCERIN; DIMETHICONE; GLYCERETH-26; DICAPRYLYL CARBONATE; PANTHENOL; MANGIFERA INDICA SEED BUTTER; LYCIUM CHINENSE FRUIT; LOWBUSH BLUEBERRY; ARCTOSTAPHYLOS UVA-URSI LEAF; LEVOMENOL; BUTYLENE GLYCOL; SOYBEAN; CERAMIDE 2; CERAMIDE 3; ALPHA-TOCOPHEROL ACETATE; GLYCYRRHIZINATE DIPOTASSIUM; HYDROGENATED PALM GLYCERIDES; DIMETHYL ETHER; CYCLOMETHICONE 5; POLYSORBATE 80; ISOHEXADECANE; CAPRYLYL GLYCOL; PHENOXYETHANOL; EDETATE DISODIUM; POTASSIUM HYDROXIDE; HEXAMETHYLINDANOPYRAN; ISOPROPYL MYRISTATE; CUCUMBER; PHENYLETHYL ALCOHOL; ROSA DAMASCENA FLOWER

StriVectin-SH NIA-114 + UVA/UVB Shields SPF 30

PARABEN-FREE, NON-COMEDOGENIC

ARTIFICIAL COLOR AND DYE FREE

Drug Facts

Active Ingredients:

Homosalate 7.5%

Octisalate 5%

Avobenzone 3%

Octocrylene 2.6%

Oxybenzone 2%

Purpose

Sunscreen

Uses:

- For prevention of sunburn

Warnings:

For external use only. When using this product, keep out of eyes. Rinse with water to remove. Stop use and ask a doctor if rash or irritation develops and lasts. For children 6 months of age or under, consult a doctor prior to use. UV exposure from the sun increases the risk of skin cancer, premature skin aging, and other skin damage. It is important to decrease UV exposure by limiting time in the sun, wearing protective clothing, and using a sunscreen.

Keep out of reach of children.

If swallowed, get medical help or contact a poison control center right away.

Directions:

- Apply a dime sized amount in the morning on cleansed face and neck or over a moisturizer.
- Reapply as needed or after towel drying, swimming or perspiring.

Inactive Ingredients:

Water (Aqua/Eau), Myristyl Nicotinate, Glycerin, Dimethicone, Nylon-12 Glycereth-26, Dicaprylyl Carbonate, Acrylates/C12-22 Alkyl Methacrylate Copolymer, Panthenol, Mangifera Indica (Mango) Seed Butter, Lycium Chinense Fruit Extract, Vaccinium Angustifolium (Blueberry) Fruit Extract, Arctostaphylos Uva Ursi Leaf Extract, Bisabolol, Butylene Glycol, Glycine Soja (Soybean) Seed Extract, Ceramide 2, Ceramide 3, Potassium Cetyl Phosphate, Glyceryl Stearate, PEG-100 Stearate, Cetyl Alcohol, PEG-11 Methyl Ether Dimethicone, Sodium Acrylate/Sodium acryloydimethyl Taurate Copolymer, Hydroxyethylcellulose, Caprylyl Glycol, Chlorophenesin, Phenoxyethanol, Disodium EDTA, Potassoium Hydroxide, Hexamethhylinanapyran, Isopropyl Myristate, Methyldihydrojasmonate 2-Isobutyl-4-Methyltetrahydro-2h-Pyran-4-01, Cucumis Sativus (cucumber)fruit extract, Phenethyl Alcohol, Methyl-A-Ionone, Rosa Damascena Flower Extract, S014

StriVectin Operating Company Inc.

New York, NY 10001

strivectin.com

2011 All Rights Reserved

For U.S. and Canadian consumer inquiries, call 1-877-722-7770.

For all other countries email: customercare@strivectin.com

Manufactured in the U.S.A.

Covered by U.S. Patent

6337065, 6552050, 6464992

Supercharged Age Protection

Sheer Enough For Every Day.

We started with a goal. Protect skin against the aging effects of the sun. So we created a powerful shield against burning UVB rays. Added the highest-rated PA protection (PA+++) against aging UVA rays. Powered up the formula with antioxidants and out propietary skin-strengthening NIA-114 technology. All in a formula so sheer you can layer it over your StriVectin-SD Intensive Concentrate for Stretch Marks and Wrinkles or moisturizer every day.

PACKAGE LABEL

Protects Against Sun Damage

New SPF 30

StriVectin-SH

NIA-114 + UVA/UVB Shields Age Protect SPF 30

365 Daily Protection

Highest PA protection from aging UVA rays; SPF30 shields against burning UV rays Long Term Benefit

Born from skin cancer prevention research, NIA-114 strengthens skin barrier to further protect against the signs of aging sun damage.